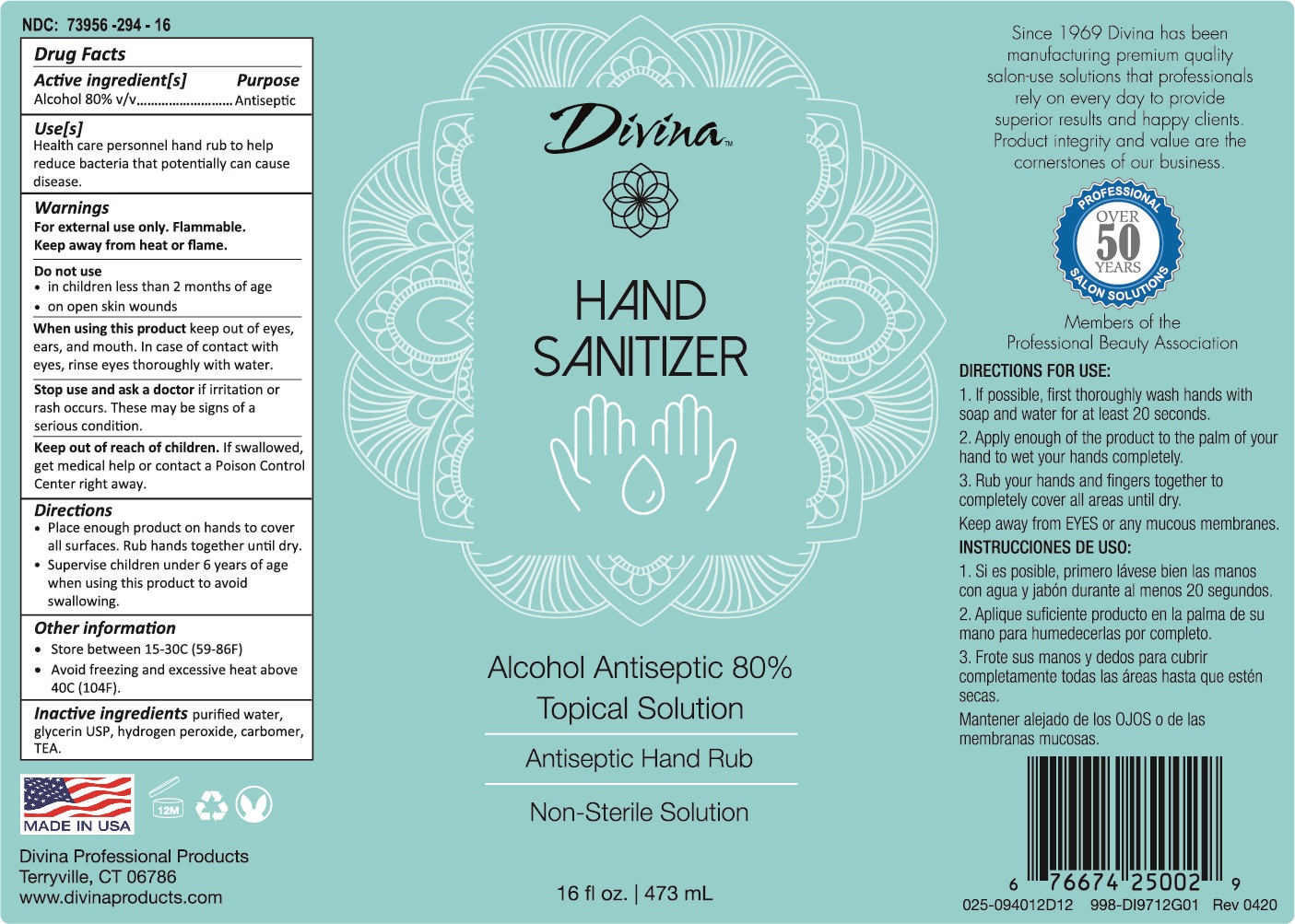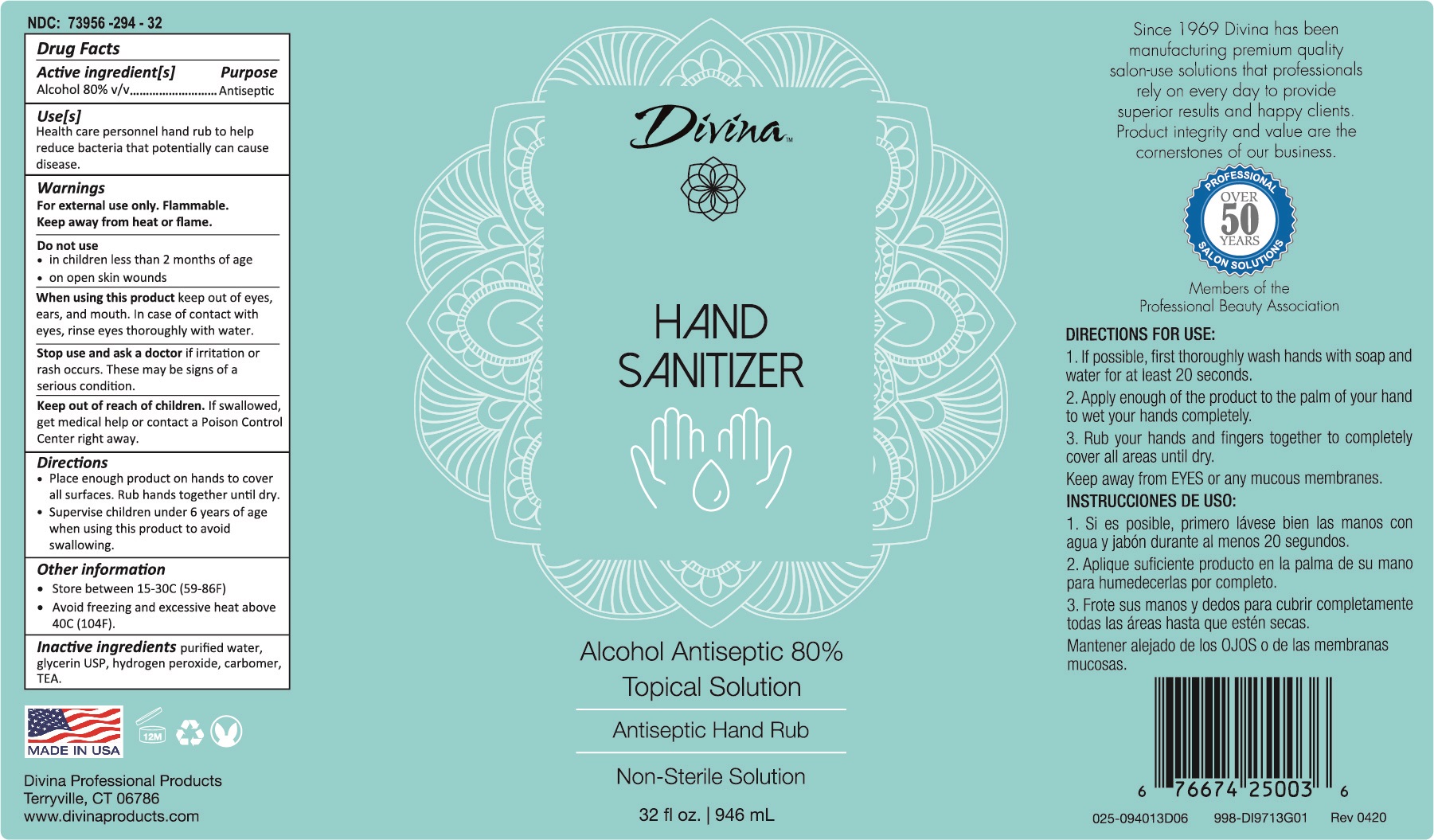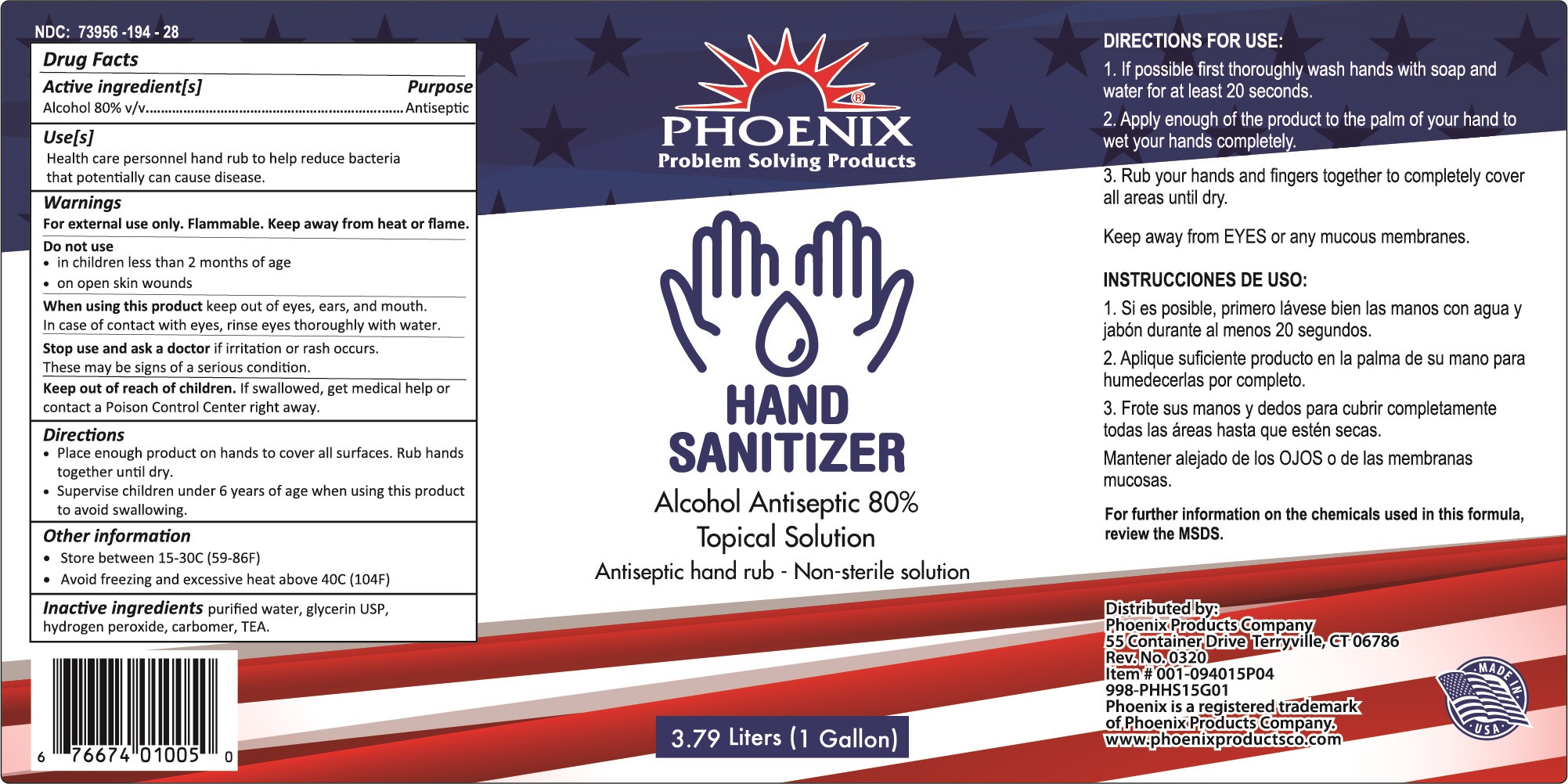 DRUG LABEL: 80% Alcohol Gel
NDC: 73956-294 | Form: SOLUTION
Manufacturer: Phoenix Products Company
Category: otc | Type: HUMAN OTC DRUG LABEL
Date: 20200825

ACTIVE INGREDIENTS: ALCOHOL 80 mL/100 mL
INACTIVE INGREDIENTS: GLYCERIN .5 mL/100 mL; HYDROGEN PEROXIDE 0.25 mL/100 mL; WATER 18.35 mL/100 mL; CARBOMER HOMOPOLYMER, UNSPECIFIED TYPE .5 mL/100 mL; TRIETHANOLAMINE LAURYL SULFATE .3 mL/100 mL

Active Ingredient(s)

Alcohol 80% v/v. Purpose: Antiseptic

Purpose

Antiseptic, Hand Rub

Use

Health care personnel hand rub to help reduce bacteria that potentially can cause disease.

Warnings

For external use only. Flammable. Keep away from heat or flame

Do not use

- in children less than 2 months of age
- on open skin wounds

When using this product keep out of eyes, ears, and mouth. In case of contact with eyes, rinse eyes thoroughly with water.

Stop use and ask a doctor if irritation or rash occurs. These may be signs of a serious condition.

Keep out of reach of children. If swallowed, get medical help or contact a Poison Control Center right away.

Directions

- Place enough product on hands to cover all surfaces. Rub hands together until dry.
- Supervise children under 6 years of age when using this product to avoid swallowing.

Other information

- Store between 15-30C (59-86F)
- Avoid freezing and excessive heat above 40C (104F)

Inactive ingredients

purified water, glycerin USP, hydrogen peroxide, carbomer, TEA.

Package Label - Principal Display Panel

[Divina 16 fl oz]

NDC: 73956-294-16

MADE IN USA
Divina Professional Products
Terryville, CT 06786
www.divinaproducts.com

HAND
SANITIZER
Alcohol Antiseptic 80%
Topical Solution
Antiseptic Hand Rub
Non-Sterile Solution
16 fl oz. | 473 mL

Since 1969 Divina has been
manufacturing premium quality
salon-use solutions that professionals
rely on every day to provide
superior results and happy clients.
Product integrity and value are the
cornerstones of our business.

Professional Salon Solutions

OVER 50 YEARS

Members of the
Professional Beauty Association

DIRECTIONS FOR USE:
1. If possible, first thoroughly wash hands with
soap and water for at least 20 seconds.
2. Apply enough of the product to the palm of your
hand to wet your hands completely.
3. Rub your hands and fingers together to
completely cover all areas until dry.
Keep away from EYES or any mucous membranes.

INSTRUCCIONES DE USO:
1. Si es posible, primero lávese bien las manos
con agua y jabón durante al menos 20 segundos.
2. Aplique suficiente producto en la palma de su
mano para humedecerlas por completo.
3. Frote sus manos y dedos para cubrir
completamente todas las áreas hasta que estén
secas.
Mantener alejado de los OJOS o de las
membranas mucosas.

6 7667425002 9

025-094012D12 998-DI9712G01 Rev 0420

Package Label - Principal Display Panel

[Divina 32 fl oz]

NDC: 73956-294-32

MADE IN USA
Divina Professional Products
Terryville, CT 06786
www.divinaproducts.com

HAND
SANITIZER
Alcohol Antiseptic 80%
Topical Solution
Antiseptic Hand Rub
Non-Sterile Solution
32 fl oz. | 946 mL

Since 1969 Divina has been
manufacturing premium quality
salon-use solutions that professionals
rely on every day to provide
superior results and happy clients.
Product integrity and value are the
cornerstones of our business.

Professional Salon Solutions

OVER 50 YEARS

Members of the
Professional Beauty Association

DIRECTIONS FOR USE:
1. If possible, first thoroughly wash hands with
soap and water for at least 20 seconds.
2. Apply enough of the product to the palm of your
hand to wet your hands completely.
3. Rub your hands and fingers together to
completely cover all areas until dry.
Keep away from EYES or any mucous membranes.

INSTRUCCIONES DE USO:
1. Si es posible, primero lávese bien las manos
con agua y jabón durante al menos 20 segundos.
2. Aplique suficiente producto en la palma de su
mano para humedecerlas por completo.
3. Frote sus manos y dedos para cubrir
completamente todas las áreas hasta que estén
secas.
Mantener alejado de los OJOS o de las
membranas mucosas.

6 7667425003 6

025-094013D06 998-DI9713G01 Rev 0420

Package Label - Principal Display Panel

[Phoenix Gallon]

NDC: 73956-194-28

6 7667401005 0

Phoenix Problem Solving Products

HAND

SANITIZER
Alcohol Antiseptic 80%
Topical Solution
Antiseptic Hand Rub - Non-Sterile Solution
3.79 Liters (1 Gallon)

DIRECTIONS FOR USE:
1. If possible, first thoroughly wash hands with
soap and water for at least 20 seconds.
2. Apply enough of the product to the palm of your
hand to wet your hands completely.
3. Rub your hands and fingers together to
completely cover all areas until dry.
Keep away from EYES or any mucous membranes.

INSTRUCCIONES DE USO:
1. Si es posible, primero lávese bien las manos
con agua y jabón durante al menos 20 segundos.
2. Aplique suficiente producto en la palma de su
mano para humedecerlas por completo.
3. Frote sus manos y dedos para cubrir
completamente todas las áreas hasta que estén
secas.
Mantener alejado de los OJOS o de las
membranas mucosas.

Distributed by:

Phoenix Products Company

55 Container Drive, Terryville, CT 06786

Rev. No 0320

Item # 001-094015P04

998-PHHS15G01

Phoenix is a registered trademark

of Phoenix Products Company.

www.phoenixproductsco.com